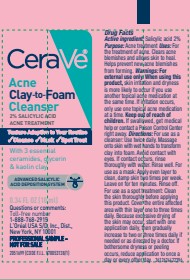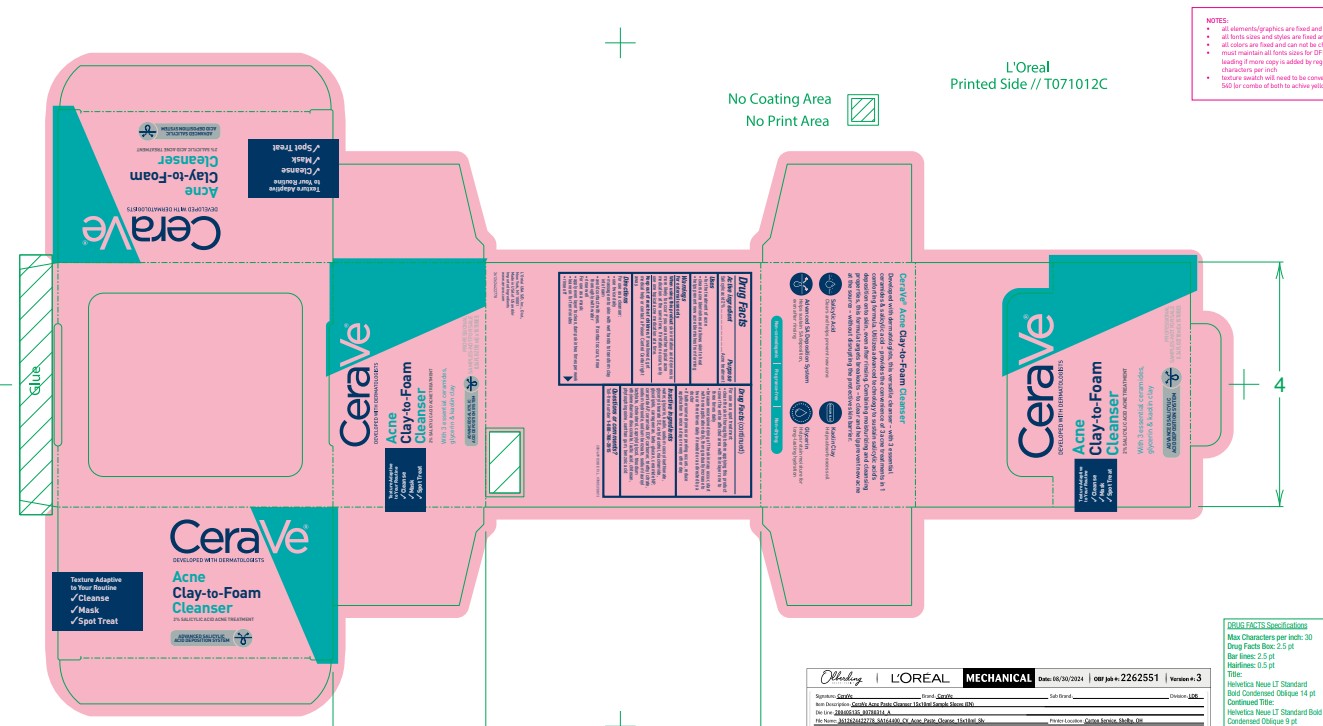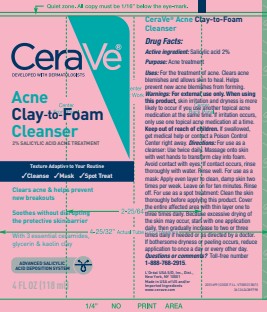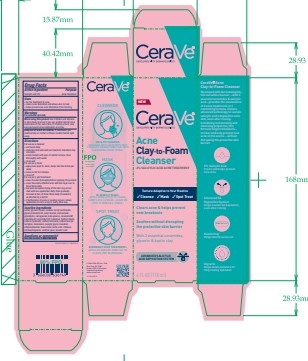 DRUG LABEL: CeraVe Acne Clay-to-Foam Cleanser
NDC: 49967-600 | Form: GEL
Manufacturer: L’Oreal USA Products Inc
Category: otc | Type: HUMAN OTC DRUG LABEL
Date: 20250626

ACTIVE INGREDIENTS: SALICYLIC ACID 20 mg/1 mL
INACTIVE INGREDIENTS: WATER; GLYCERIN; KAOLIN; SODIUM COCOYL ISETHIONATE; GLYCERYL STEARATE SE; CETYL ALCOHOL; NIACINAMIDE; CARRAGEENAN; CERAMIDE NP; CERAMIDE AP; YEAST .BETA.-D-GLUCAN; CARBOMER; TRIETHYL CITRATE; SODIUM HYDROXIDE; SODIUM BENZOATE; SODIUM LAUROYL LACTYLATE; CHOLESTEROL; CAPRYLYL GLYCOL; TRISODIUM ETHYLENEDIAMINE DISUCCINATE; LACTIC ACID; PHYTOSPHINGOSINE; XANTHAN GUM; BENZOIC ACID; POLIGLUSAM

Drug Facts

Active ingredient

Salicylic acid 2%

Purpose

Acne treatment

Uses

• for the treatment of acne
• clears acne blemishes and allows skin to heal
• helps prevent new acne blemishes from forming

Warnings

For external use only

When using this product

skin irritation and dryness
is more likely to occur if you use another topical acne
medication at the same time. If irritation occurs, only
use one topical acne medication at a time.

Keep out of reach of children.

If swallowed, get
medical help or contact a Poison Control Center right away.

Directions

For use as a cleanser:
• use twice daily
• massage onto skin with wet hands to transform clay
into foam
• avoid contact with eyes. If contact occurs, rinse
thoroughly with water
• rinse well
For use as a mask:
• apply even layer to clean, damp skin two times per
week
• leave on for ten minutes
• rinse off
For use as a spot treatment:
• clean the skin thoroughly before applying this product
• cover the entire affected area with thin layer one to
three times daily
• because excessive drying of the skin may occur,
start with one application daily, then gradually
increase to two or three times daily if needed or
as directed by a doctor
• if bothersome dryness or peeling occurs, reduce
application to once a day or every other day

Inactive ingredients

water, glycerin, kaolin, sodium cocoyl isethionate,
glyceryl stearate SE, cetyl alcohol, niacinamide,
glycolipids, carrageenan, beta-glucan, ceramide NP,
ceramide AP, ceramide EOP, carbomer, triethyl citrate,
sodium hydroxide, sodium benzoate, sodium lauroyl
lactylate, cholesterol, caprylyl glycol, trisodium
ethylenediamine disuccinate, lactic acid, chitosan,
phytosphingosine, xanthan gum, benzoic acid

Questions or comments?

Toll-free number 1-888-768-2915